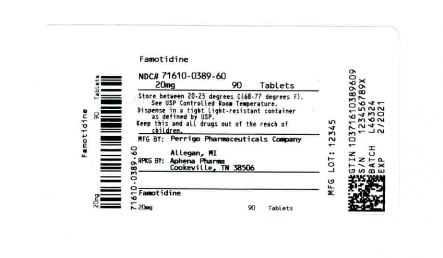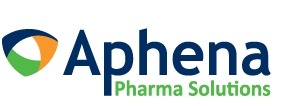 DRUG LABEL: Basic Care famotidine
NDC: 71610-389 | Form: TABLET, FILM COATED
Manufacturer: Aphena Pharma Solutions - Tennessee, LLC
Category: otc | Type: HUMAN OTC DRUG LABEL
Date: 20200219

ACTIVE INGREDIENTS: FAMOTIDINE 20 mg/1 1
INACTIVE INGREDIENTS: CARNAUBA WAX; SILICON DIOXIDE; CROSCARMELLOSE SODIUM; LACTOSE MONOHYDRATE; MAGNESIUM STEARATE; CELLULOSE, MICROCRYSTALLINE; POLYETHYLENE GLYCOL; POLYVINYL ALCOHOL; TALC; TITANIUM DIOXIDE

Famotidine Tablets 20 mg Drug Facts

Active ingredient (in each tablet)

Famotidine 20 mg

Purpose

Acid reducer

Uses

- relieves heartburn associated with acid indigestion and sour stomach
- prevents heartburn associated with acid indigestion and sour stomach brought on by eating or drinking certain food and beverages

Warnings

Allergy alert: Do not use if you are allergic to famotidine or other acid reducers

Do not use

- if you have trouble or pain swallowing food, vomiting with blood, or bloody or black stools. These may be signs of a serious condition. See your doctor.
- if you have kidney disease, except under the advice and supervision of a doctor
- with other acid reducers

Ask a doctor before use if you have

- had heartburn over 3 months. This may be a sign of a more serious condition.
- heartburn with lightheadedness, sweating, or dizziness
- chest pain or shoulder pain with shortness of breath; sweating; pain spreading to arms, neck or shoulders; or lightheadedness
- frequent chest pain
- frequent wheezing, particularly with heartburn
- unexplained weight loss
- nausea or vomiting
- stomach pain

Stop use and ask a doctor if

- your heartburn continues or worsens
- you need to take this product for more than 14 days

If pregnant or breast-feeding,

ask a health professional before use.

Keep out of reach of children.

In case of overdose, get medical help or contact a Poison Control Center right away.

Directions

- adults and children 12 years and over:
- to relieve symptoms, swallow 1 tablet with a glass of water. Do not chew.
- to prevent symptoms, swallow 1 tablet with a glass of water at any time from 10 to 60 minutesbefore eating food or drinking beverages that cause heartburn
- do not use more than 2 tablets in 24 hours
- children under 12 years: ask a doctor

Other information

- read the directions and warnings before use
- keep the carton. It contains important information.
- store at 20°-25°C (68°-77°F)
- protect from moisture and light

Inactive ingredients

carnauba wax, colloidal silicon dioxide, croscarmellose sodium, lactose (monohydrate), magnesium stearate, microcrystalline cellulose, polyethylene glycol, polyvinyl alcohol, talc, and titanium dioxide

Repackaging Information

Please reference the How Supplied section listed above for a description of individual tablets. This drug product has been received by Aphena Pharma - TN in a manufacturer or distributor packaged configuration and repackaged in full compliance with all applicable cGMP regulations. The package configurations available from Aphena are listed below:

Count | 20 mg
90 | 71610-389-60

Store between 20°-25°C (68°-77°F). See USP Controlled Room Temperature. Dispense in a tight light-resistant container as defined by USP. Keep this and all drugs out of the reach of children.

Repackaged by:
Cookeville, TN 38506
20200219JH

PRINCIPAL DISPLAY PANEL - 20 mg

NDC 71610-389 - Famotidine, USP 20 mg Tablets